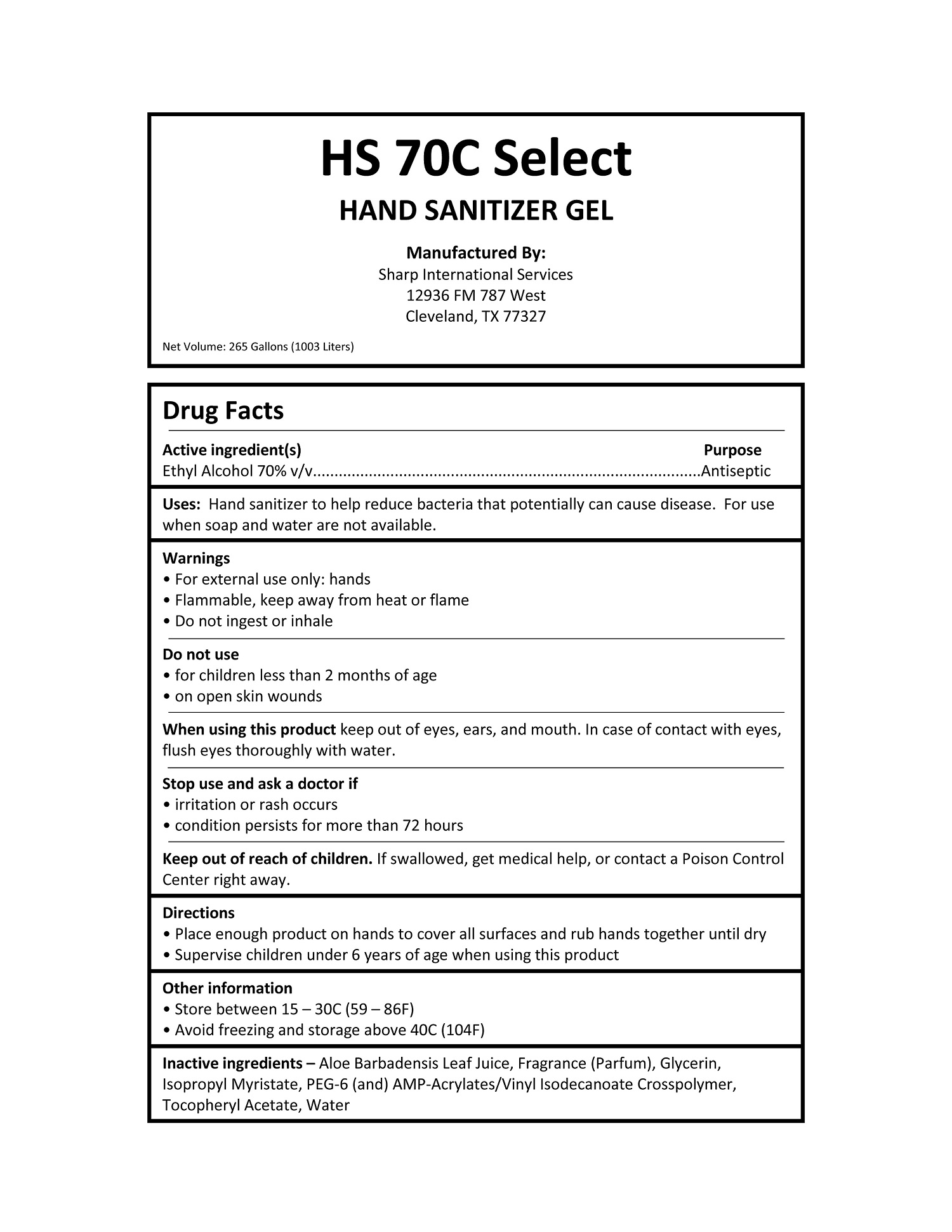 DRUG LABEL: HS-70C SELECT Handsanitizer
NDC: 74221-007 | Form: GEL
Manufacturer: Sharp International Services, LLC
Category: otc | Type: HUMAN OTC DRUG LABEL
Date: 20200901

ACTIVE INGREDIENTS: ALCOHOL 0.7 L/1 L
INACTIVE INGREDIENTS: WATER; GLYCERIN; RAPIDGEL EZ1; ALOE VERA LEAF; ISOPROPYL MYRISTATE; .ALPHA.-TOCOPHEROL ACETATE, DL-

HS 70C SELECT HANDSANITIZER SHARP INTERNATIONAL

Drug Active

Active Ingredients | Purpose
Ethyl Alcohol 70%v/v | Antiseptic

Uses:

- Hand sanitizer to help reduce bacteria that potentially can cause disease.
- For use when soap and water are not available.

Stop Use amd ask a doctor if

- irritation or rash occurs
- condition persists for more than 72 hours

Do not use

- For children less than 2 months of age
- on open skin wounds

Keep out of reach of children

If swallowed, get medical help, or contact a Posion ControlCenter Right Away

Uses:

Handsanitizer to help reduce bacteria that potentially can cause disease. For use when soap and wateer are not available

Warnings

- For external use only : hands
- Flammable keep away from heat or flame
- Do not ingest or inhale

Stop use and ask a doctor if

- irritation or rash occurs
- condition persists for more than 72 hours

STORAGE AND HANDLING

- Store between 15 - 30C (59 - 86 F)
- Avoidfreezing and storage above 40C (140F)

INACTIVE INGREDIENT

Aloe Barbadensis Leaf Juice

Fragrance

Glycerin

Isopropyl Myristate

PEG-6 and AMP - Acrylatees/ Vinyl Isodecanoate Crosspolymer

Water